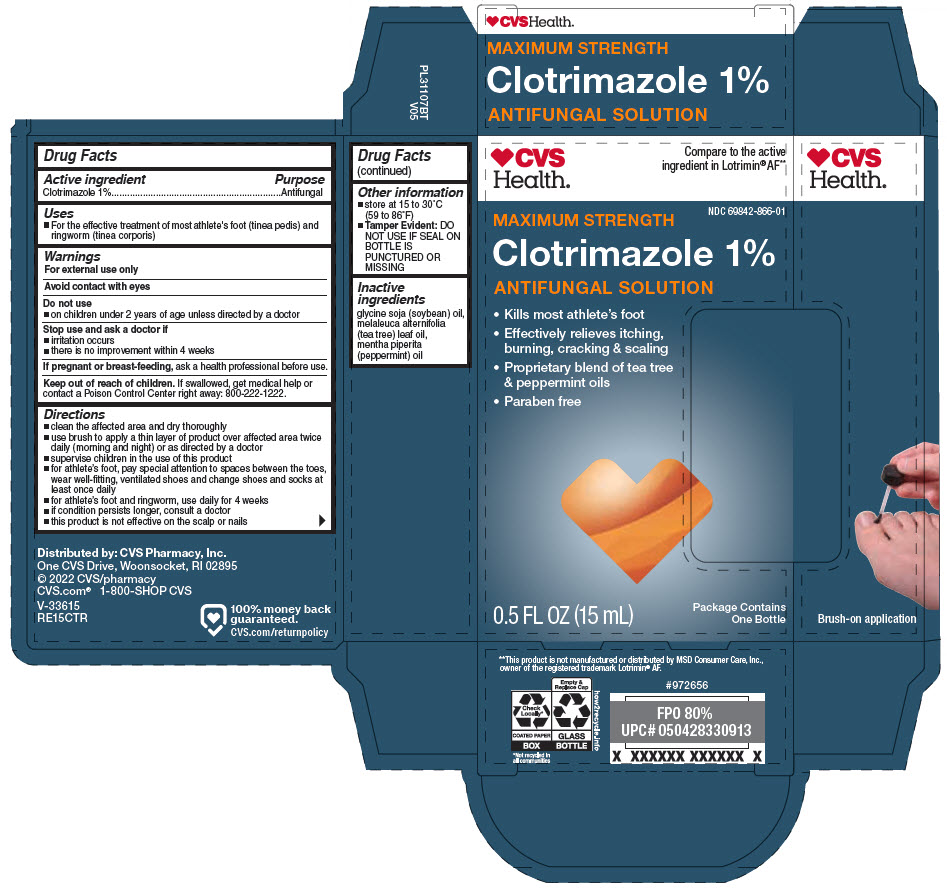 DRUG LABEL: CVS Clotrimazole 
NDC: 69842-866 | Form: SOLUTION
Manufacturer: CVS Pharmacy
Category: otc | Type: HUMAN OTC DRUG LABEL
Date: 20221101

ACTIVE INGREDIENTS: CLOTRIMAZOLE 10 mg/1 mL
INACTIVE INGREDIENTS: SOYBEAN OIL; PEPPERMINT OIL; TEA TREE OIL

CVS Clotrimazole 1% Solution
Maximum Strength

Drug Facts

Active ingredient

Clotrimazole 1%

Purpose

Antifungal

Uses

- For the effective treatment of most athlete's foot (tinea pedis) and ringworm (tinea corporis)

Warnings

For external use only

Avoid contact with eyes

Do not use

- on children under 2 years of age unless directed by a doctor

Stop use and ask a doctor if

- irritation occurs
- there is no improvement within 4 weeks

PREGNANCY OR BREAST FEEDING

If pregnant or breast-feeding, ask a health professional before use.

Keep out of reach of children. If swallowed, get medical help or contact a Poison Control Center right away: 800-222-1222.

Directions

- clean the affected area and dry thoroughly
- use brush to apply a thin layer of product over affected area twice daily (morning and night) or as directed by a doctor
- supervise children in the use of this product
- for athlete's foot, pay special attention to spaces between the toes, wear well-fitting, ventilated shoes and change shoes and socks at least once daily
- for athlete's foot and ringworm, use daily for 4 weeks
- if condition persists longer, consult a doctor
- this product is not effective on the scalp or nails

Other information

- store at 15 to 30°C (59 to 86°F)
- Tamper Evident: DO NOT USE IF SEAL ON BOTTLE IS PUNCTURED OR MISSING

Inactive ingredients

glycine soja (soybean) oil, melaleuca alternifolia (tea tree) leaf oil, mentha piperita (peppermint) oil

Distributed by: CVS Pharmacy, Inc.
One CVS Drive, Woonsocket, RI 02895

PRINCIPAL DISPLAY PANEL - 15 mL Bottle Carton

CVS
Health®

Compare to the active
ingredient in Lotrimin®AF**

NDC 69842-866-01

MAXIMUM STRENGTH
Clotrimazole 1%
ANTIFUNGAL SOLUTION

- Kills most athlete's foot
- Effectively relieves itching,
  burning, cracking & scaling
- Proprietary blend of tea tree
  & peppermint oils
- Paraben free

Package Contains
One Bottle

0.5 FL OZ (15 mL)